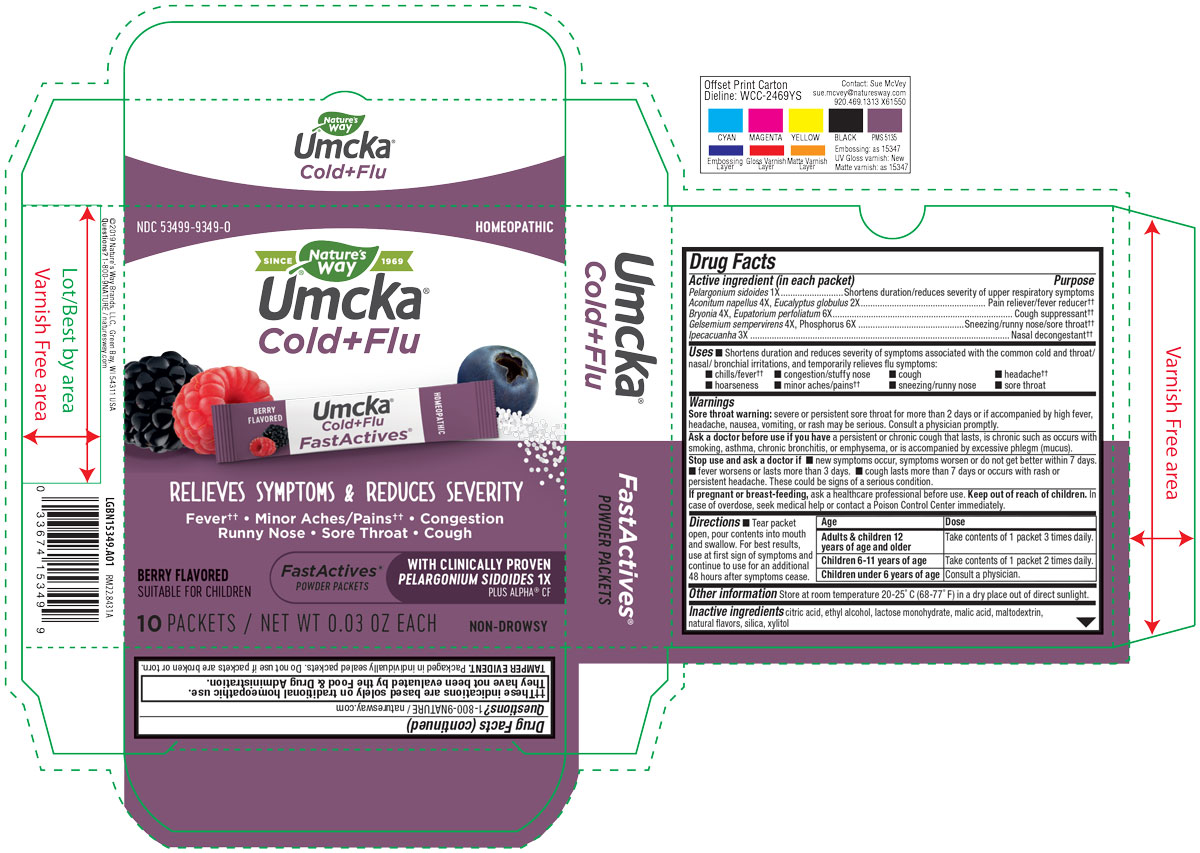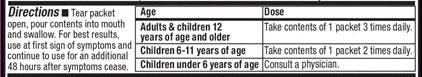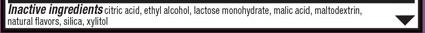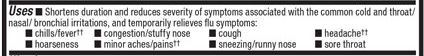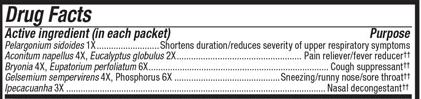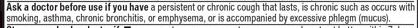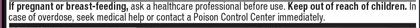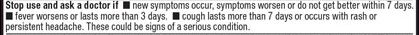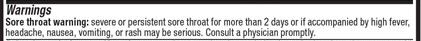 DRUG LABEL: Umcka Fastactv Berry
NDC: 83102-9349 | Form: POWDER
Manufacturer: ProSolutions Inc
Category: homeopathic | Type: HUMAN OTC DRUG LABEL
Date: 20250410

ACTIVE INGREDIENTS: EUCALYPTUS GLOBULUS LEAF 2 [hp_X]/1 1; PHOSPHORUS 6 [hp_X]/1 1; IPECAC 3 [hp_X]/1 1; BRYONIA ALBA ROOT 4 [hp_X]/1 1; EUPATORIUM PERFOLIATUM FLOWERING TOP 6 [hp_X]/1 1; GELSEMIUM SEMPERVIRENS ROOT 4 [hp_X]/1 1; PELARGONIUM SIDOIDES ROOT 1 [hp_X]/1 1; ACONITUM NAPELLUS 4 [hp_X]/1 1
INACTIVE INGREDIENTS: MALTODEXTRIN; ALCOHOL; XYLITOL; SILICON DIOXIDE; MALIC ACID; LACTOSE MONOHYDRATE; CITRIC ACID MONOHYDRATE

Recent Major Changes

Dosage & Administration, Warnings, Indications and Usage, added for initial submission in 12/2022.

When expiring marketing dates in version 2, SPL could not find original file file name that included an & in file name.

Keep out of reach of children.